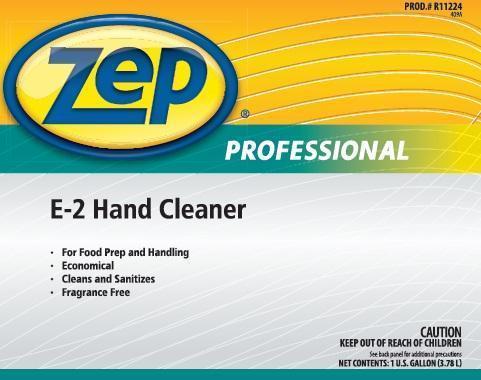 DRUG LABEL: Zep Professional E-2 Hand Cleaner
NDC: 66949-112 | Form: LIQUID
Manufacturer: Zep Inc.
Category: otc | Type: HUMAN OTC DRUG LABEL
Date: 20131205

ACTIVE INGREDIENTS: BENZALKONIUM CHLORIDE .013 g/10 mL
INACTIVE INGREDIENTS: WATER; COCAMIDOPROPYL BETAINE; DIDECYLDIMETHYLAMMONIUM CHLORIDE; PEG-6 COCAMIDE; ALCOHOL; HYDROXYETHYL CELLULOSE (2000 CPS AT 1%); DMDM HYDANTOIN; IODOPROPYNYL BUTYLCARBAMATE; GLUTARAL; ANHYDROUS CITRIC ACID

Zep Professional E-2 Hand Cleaner

Active ingredient

Benzalkonium chloride 0.13%

Purpose

Antiseptic Handwash

Uses

- Hand sanitizing to decrease bacteria on skin
- For use in food processing facilities

Warnings

For external use only.

DO NOT USE

Can cause eye irritation. Avoid contact with eyes.

When using this product

- Do not use in or around eyes. If eye contact occurs, rinse well with water for at least 15 minutes. Consult a physician.
- Do no swallow this product. If swallowed, do not induce vomiting. If individual is conscious, give large quantities of water to drink and consult a physician immediately.

STOP USE

Discontinue use if irritation and redness develops. If condition persists for more than 72 hours, consult a doctor.

Keep out of reach of children.

Directions

- Wet hands with water
- Dispense one or two squirts in palm of hand
- Massag soap into hands and wrists, emphasizing back of hands, knuckles and cuticles
- Hands must be thoroughly rinsed with potable water

Other information

- Keep container closed
- Store at room temperature
- Do not freeze
- Do not reuse empty container
- Dispose in accordance with all applicable federal, state & local regulations

Inactive ingredients

Water, Cocamidopropyl Betaine, Didecyldimethylammonium Chloride, PEG-6 Cocamide, Ethanol, Hydroxyethylcellusolose, DMDM Hydantoin (and) Iodopropynyl Butylcarbamate, Citric Acid